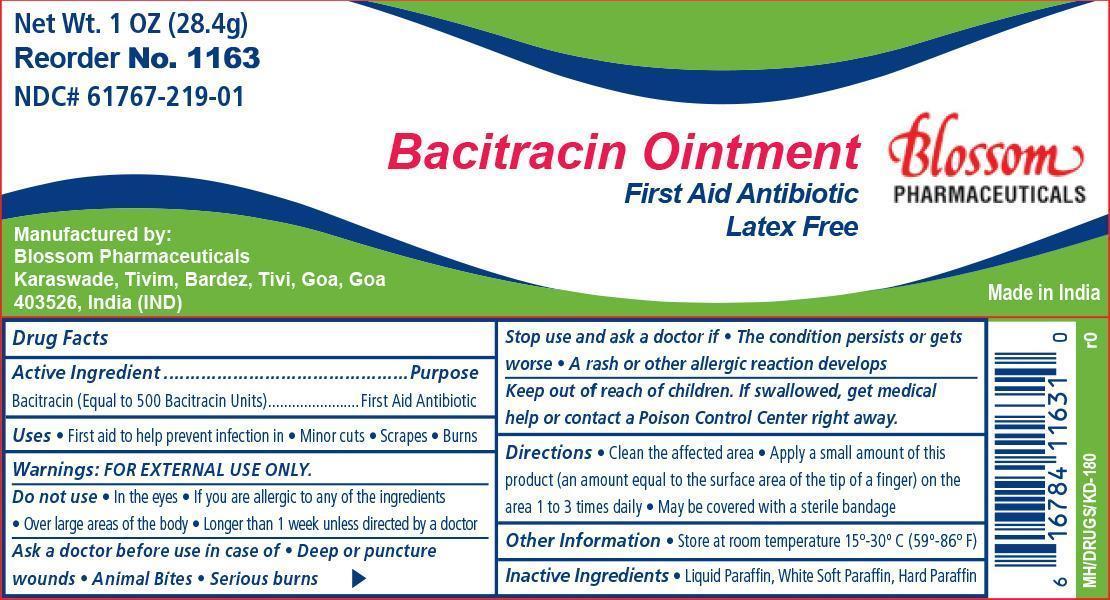 DRUG LABEL: Bacitracin
NDC: 61767-219 | Form: OINTMENT
Manufacturer: Blossom Pharmaceuticals
Category: otc | Type: HUMAN OTC DRUG LABEL
Date: 20140306

ACTIVE INGREDIENTS: BACITRACIN 500 [iU]/1 g
INACTIVE INGREDIENTS: MINERAL OIL; PETROLATUM

Bacitracin Ointment

Active ingredient Purpose
Bacitracin Zinc (Equal to 500 Bacitracin Units) First Aid Antibiotic

Purpose:

First aid to help prevent infection.

Warnings:

For external use only

Dosage and Administration

Directions:

- clean the affected areas
- apply a small amount of product (an amountb equal to the surface area of the tip of the finger) on the area 1 to 3 times daily.
- may be covered with a sterile bandage

Indications and Usage

First aid to help prevent infection in:

- minor cuts
- scrapes
- burns

Stop Use and ask a doctor if:

- the condition persists or gets worse, or if a rash or other allergic reaction develops.

Do Not Use if:

- if you are allergic to any of the ingredients
- in the eyes
- over large areas of the body
- longer than 1 week unless directed by a doctor

Ask a doctor before use:

- in case of deep or puncture wounds
- animal bites
- serious burns

Keep out of reach of children

- If swallowed, get medical help or contact a Poison Control Center right away

Other information

- store at controlled room temperature 15°-30° C (59°-86° F)

Inactive ingredients

Light Mineral Oil, White Petrolatum

Principal Display Panel

Bacitracin Ointment

BP Bacitracin.jpg